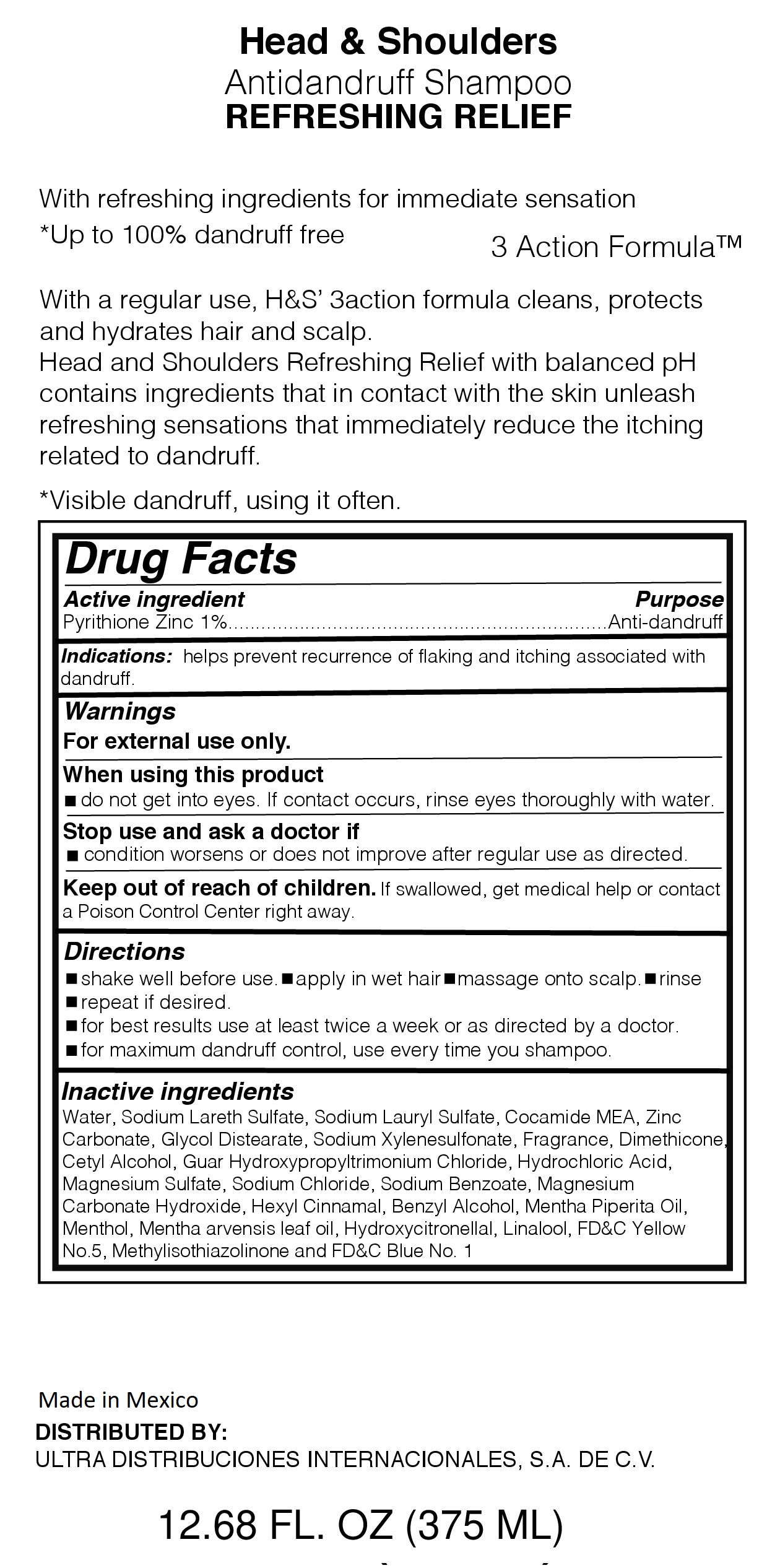 DRUG LABEL: HEAD AND SHOULDERS REFRESHING RELIEF
NDC: 72389-108 | Form: LOTION/SHAMPOO
Manufacturer: ULTRA DISTRIBUCIONES INTERNACIONALES, S.A. DE C.V.
Category: otc | Type: HUMAN OTC DRUG LABEL
Date: 20220114

ACTIVE INGREDIENTS: PYRITHIONE ZINC 1 g/100 mL
INACTIVE INGREDIENTS: COCO MONOETHANOLAMIDE; MENTHA PIPERITA; HYDROXYCITRONELLAL; FD&C YELLOW NO. 5; FD&C BLUE NO. 1; MENTHOL, UNSPECIFIED FORM; SODIUM LAURYL SULFATE; SODIUM LAURETH SULFATE; GLYCOL DISTEARATE; LINALOOL, (-)-; MAGNESIUM CARBONATE HYDROXIDE; DIMETHICONE; .ALPHA.-HEXYLCINNAMALDEHYDE; SODIUM CHLORIDE; SODIUM XYLENESULFONATE; METHYLISOTHIAZOLINONE; SODIUM BENZOATE; GUAR HYDROXYPROPYLTRIMONIUM CHLORIDE (1.7 SUBSTITUENTS PER SACCHARIDE); HYDROCHLORIC ACID; ZINC CARBONATE; CETYL ALCOHOL; BENZYL ALCOHOL; MAGNESIUM SULFATE, UNSPECIFIED; MENTHA ARVENSIS LEAF OIL; WATER

Head and Shoulders Refreshing Relief

Purpose

With refreshing ingredients for immediate sensation

*up to 100% dandruff free

With Regular use, H&S 3action formula cleans, protects and hydrates hair and scalf.

Head and Shoulders Refreshing Relief with balanced PH contains ingredients that in contact with the skin unleash refreshing sensations that immediate reduce the itching related to dandruff

*Visible dandruff, using it often.

Active Ingredient

Active Ingredient................................................................................Purpose

Pyrithione Zinc 1%.....................................................................Anti-dandruff

Indications:

helps prevent recurrence of flaking and itching associated with dandruff

Warnings

for external use only.

When using this product

-do not get into eyes. If contact occurs, rinse thoroughly with water

Stop use and ask doctor if

condition worsens or does not improve after regular use as directed

Keep our of reach of children

If swallowed, get medical help or contact a Poison Control Center right away

Directions

-shake well before use - apply in wet hair - massage into scalp - rinse

-repeat as desired

-for best results use at least twice a week or as directed by a doctor

-for maximum dandruff control, use every time you shampoo

Inactive Ingredients

Water, Sodium Laureth Sulfate,Sodium Lauryl Sulfate, Cocamide MEA, Zinc Carbonate,

Glycol distearate,sodium xylenesulfonate, Fragrance, Dimethicone, Cetyl Alcohol, Guar Hydroxypropyltrimonium Chloride,

Hydrochloric Acid, Magnesium Sulfate, Sodium Chloride, Sodium Benzoate, Magnesium Carbonate Hydroxide,

Hexyl Cinnamal, Benzyl Alcohol, Mentha Piperita Oil, Menthol, Mentha arvensis leaf oil, Hydroxycitronellal, Linalool,

FD&C Yellow No. 5, Methylisothiaolinone, FD&C Blue No. 1

Distributed by:

ULTRA DISTRIBUCIONES INTERNACIONALES, S.A. DE C.V.

Made in Mexico

HEAD & SHOULDERS Antidandruff Shampoo REFRESHING RELIEF

Refreshing Relief